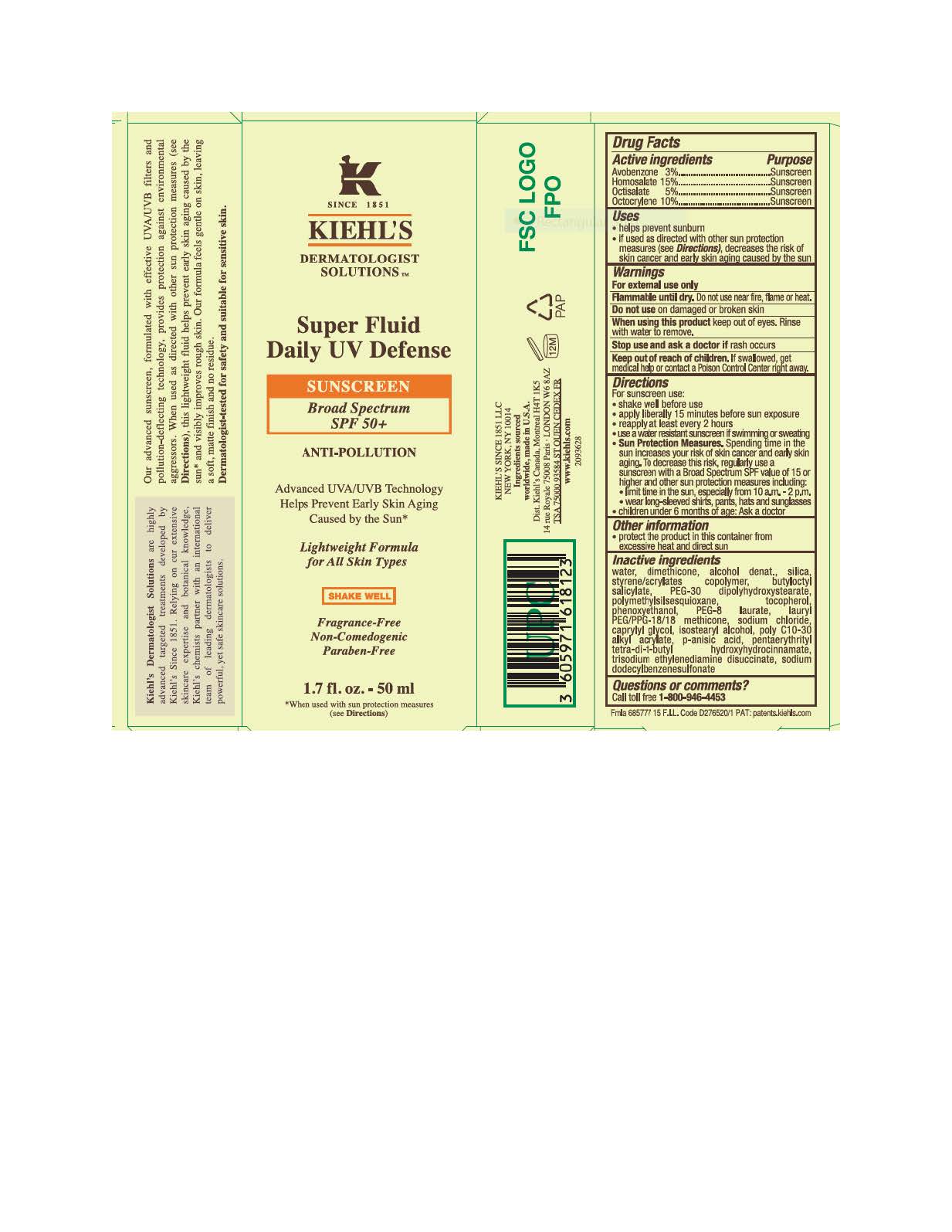 DRUG LABEL: Kiehls Since 1851 Dermatologist Solutions Super Fluid Daily UV Defense Broad Spectrum SPF 50 plus Sunscreen Antipollution Lightweight Formula
NDC: 49967-812 | Form: LOTION
Manufacturer: L'Oreal USA Products Inc.
Category: otc | Type: HUMAN OTC DRUG LABEL
Date: 20231230

ACTIVE INGREDIENTS: AVOBENZONE 30 mg/1 mL; HOMOSALATE 150 mg/1 mL; OCTISALATE 50 mg/1 mL; OCTOCRYLENE 100 mg/1 mL
INACTIVE INGREDIENTS: WATER; DIMETHICONE; ALCOHOL; SILICON DIOXIDE; STYRENE/ACRYLAMIDE COPOLYMER (500000 MW); BUTYLOCTYL SALICYLATE; PEG-30 DIPOLYHYDROXYSTEARATE; POLYMETHYLSILSESQUIOXANE (4.5 MICRONS); TOCOPHEROL; PHENOXYETHANOL; PEG-8 LAURATE; LAURYL PEG/PPG-18/18 METHICONE; SODIUM CHLORIDE; CAPRYLYL GLYCOL; ISOSTEARYL ALCOHOL; P-ANISIC ACID; PENTAERYTHRITOL TETRAKIS(3-(3,5-DI-TERT-BUTYL-4-HYDROXYPHENYL)PROPIONATE); TRISODIUM ETHYLENEDIAMINE DISUCCINATE; SODIUM DODECYLBENZENESULFONATE

Drug Facts

Active ingredients

Avobenzone 3%

Homosalate 15%

Octisalate 5%

Octocrylene 10%

Purpose

Sunscreen

Uses

- helps prevent sunburn
- if used as directed with other sun protection measures (see Directions), decreases the risk of skin cancer and early skin aging caused by the sun

Warnings

For external use only

Flammble until dry. Do not use near fire, flame or heat.

Do not use

on damaged or broken skin

When using this product

keep out of eyes. Rinse with water to remove.

Stop use and ask a doctor if

rash occurs

Keep out of reach of children.

If swallowed, get medical help or contact a Poison Control Center right away.

Directions

- shake well before use
- apply liberally 15 minutes before sun exposure
- reapply at least every 2 hours
- use a water resistant sunscreen if swimming or sweating
- Sun Protection Measures. Spending time in the sun increases your risk of skin cancer and early skin aging. To decrease this risk, regularly use a sunscreen with a Broad Spectrum SPF value of 15 or higher and other sun protection measures including:
- limit time in the sun, especially from 10 a.m. - 2p.m.
- wear long-sleeved shirts, pants, hats and sunglasses
- children under 6 months of age: Ask a doctor

Other information

- protect the product in this container from excessive heat and direct sun

Inactive ingredients

water, dimethicone, alcohol denat., silica, styrene/acrylates copolymer, butyloctyl salicylate, PEG-30 dipolyhydroxystearate, polymethylsilsesquioxane, tocopherol, phenoxyethanol, PEG-8 laurate, lauryl PEG/PPG-18/18 methicone, sodium chloride, caprylyl glycol, isostearyl alcohol, poly c10-30 alkyl acrylate, p-anisic acid, pentaerythrityl tetra-di-t-butyl hydroxyhydrocinnamate, trisodium ethylenediamine disuccinate, sodium dodecylbenzenesulfonate